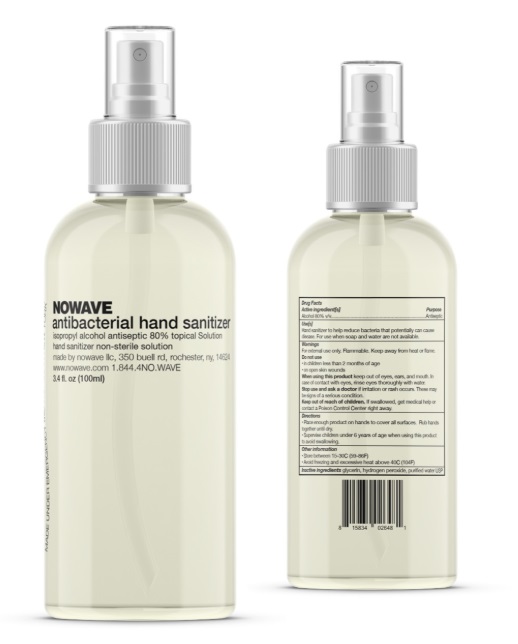 DRUG LABEL: NOWAVE HAND SANITIZER
NDC: 74036-001 | Form: GEL
Manufacturer: NOWAVE LLC
Category: otc | Type: HUMAN OTC DRUG LABEL
Date: 20200327

ACTIVE INGREDIENTS: ALCOHOL 48 mL/60 mL
INACTIVE INGREDIENTS: HYDROGEN PEROXIDE 0.075 mL/60 mL; GLYCERIN 0.87 mL/60 mL; WATER 11.12 mL/60 mL

DRUG FACTS LABEL

Drug Facts Active ingredient[s] Purpose Alcohol 80% v/v.………………………………………….………….……….….……………………………………………...............................................Antiseptic Use[s] Hand sanitizer to help reduce bacteria that potentially can cause disease. For use when soap and water are not available. Warnings For external use only. Flammable. Keep away from heat or flame Do not use • in children less than 2 months of age • on open skin wounds When using this product keep out of eyes, ears, and mouth. In case of contact with eyes, rinse eyes thoroughly with water. Stop use and ask a doctor if irritation or rash occurs. These may be signs of a serious condition. Keep out of reach of children. If swallowed, get medical help or contact a Poison Control Center right away. Directions • Place enough product on hands to cover all surfaces. Rub hands together until dry. • Supervise children under 6 years of age when using this product to avoid swallowing. Other information • Store between 15-30C (59-86F) • Avoid freezing and excessive heat above 40C (104F) Inactive ingredients glycerin, hydrogen peroxide, purified water USP

WARNINGS

For external use only. Flammable. Keep away from heat or flame.

ACTIVE INGREDIENT

Alcohol 80% v/v ............Anitseptic

Do not use
in children less than 2 months of age
on open skin wounds

When using this product, keep out of eyes, ears, and mouth. In case of contact with eyes, rinse eyes thoroughly with water.

Stop use and ask a doctor if irritation or rash occurs. this may be a sign of a serious condition.

Keep out of reach of children. If swallowed, get medical help or contact a Poison Control Center immediately.

INACTIVE INGREDIENT

Glycerin, hydrogen peroxide, purified water USP

INDICATIONS AND USAGE

Use(s)

Hand sanitizer to help reduce bacteria that can cause disease. For use when soap and water are not available.

PURPOSE

Hand sanitizer to help reduce bacteria that potentially can cause disease. For use when soap and water are not available.

Directions
place enough product on hands to cover all surfaces. Rub hands together until dry.
Supervise Children under 6 years of age to prevent swallowing.

PACKAGE LABEL

Alcohol Antiseptic 80% Topical Solution Hand Sanitizer Non-sterile Solution [Insert Volume of Product in mL